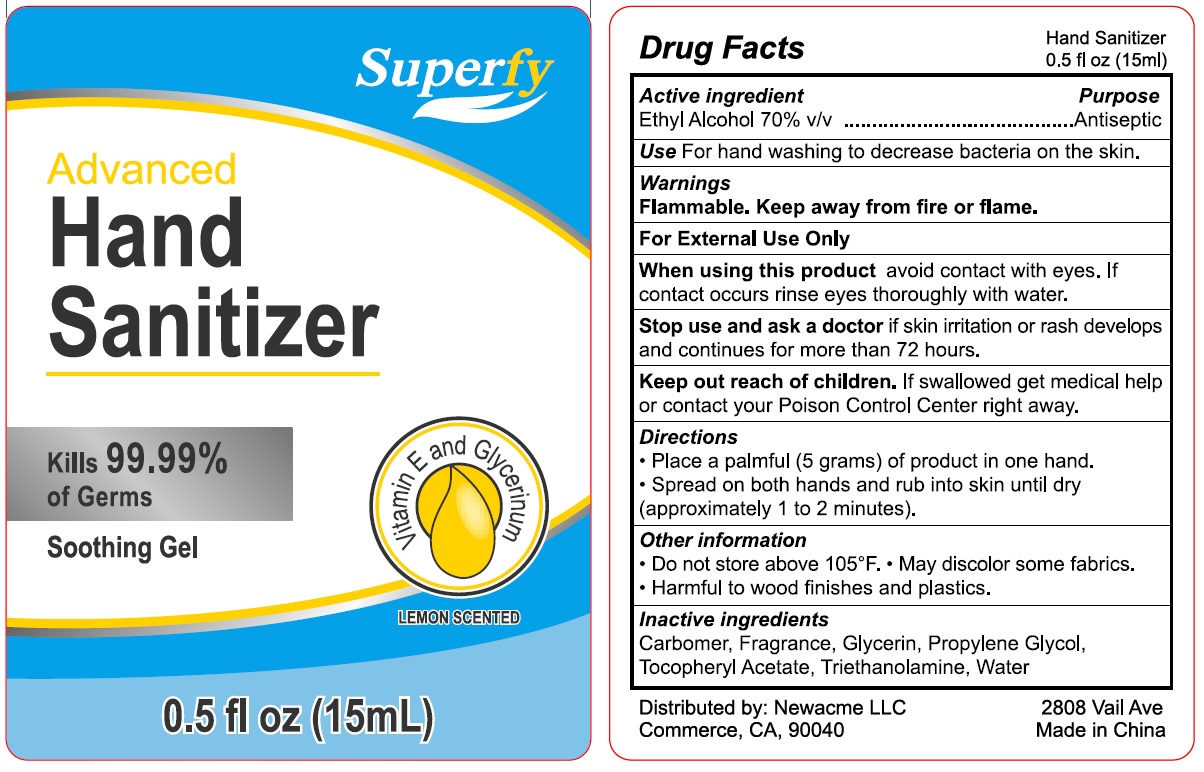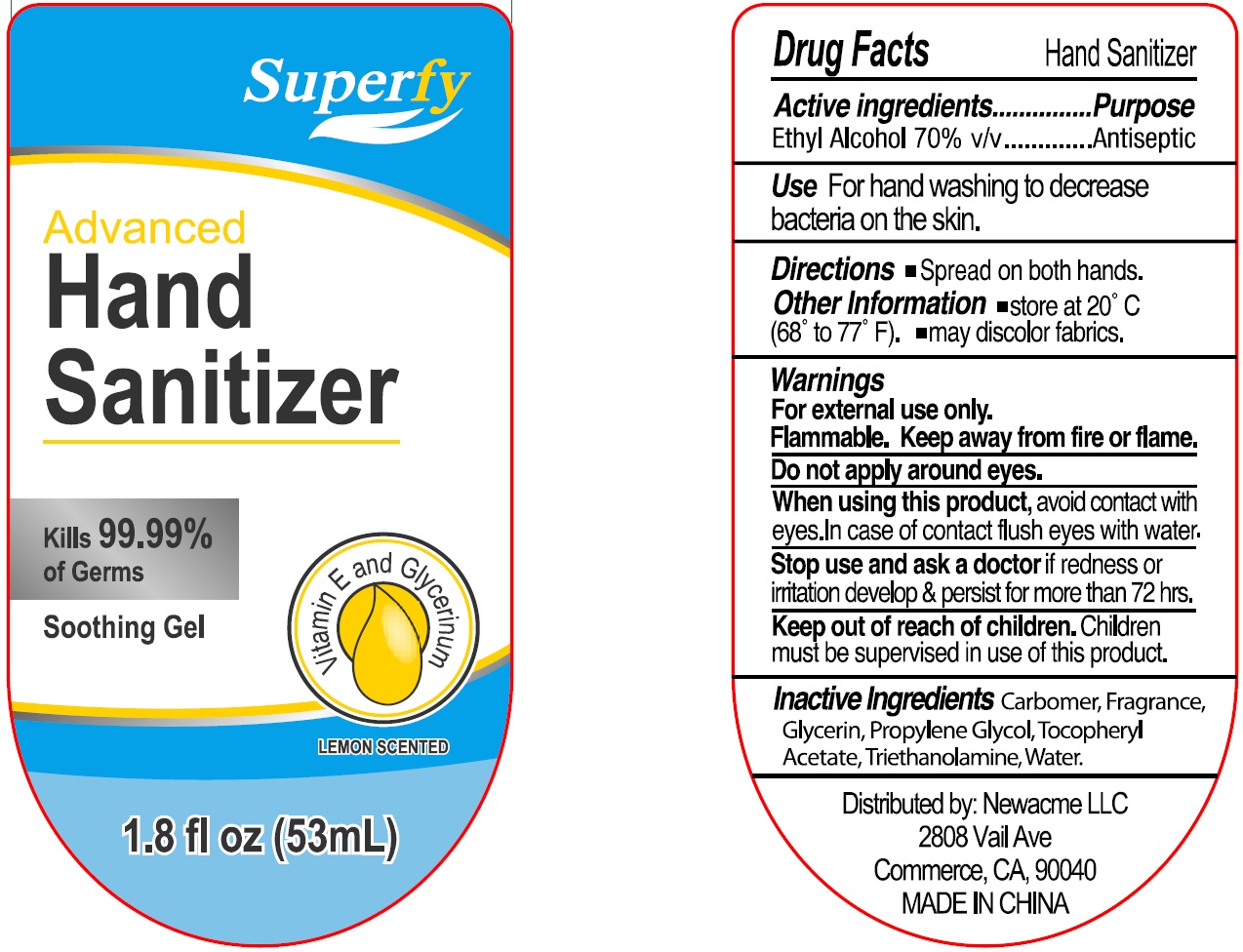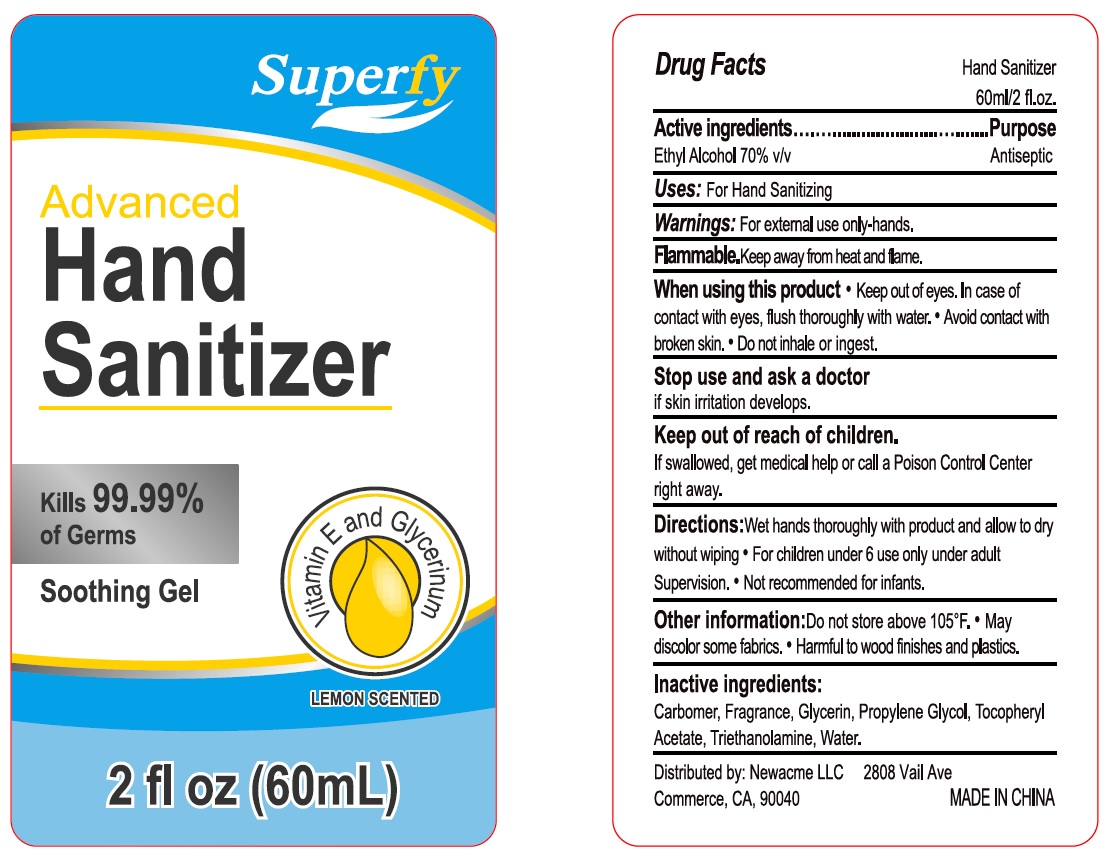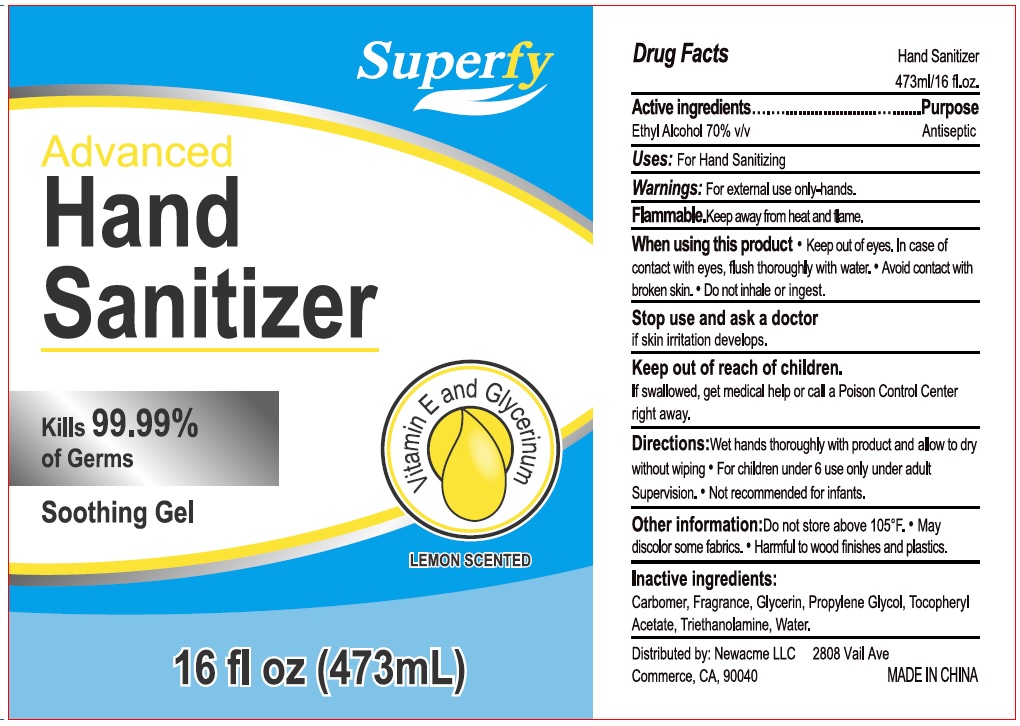 DRUG LABEL: Hand Sanitizer
NDC: 74341-194 | Form: GEL
Manufacturer: Newacme llc
Category: otc | Type: HUMAN OTC DRUG LABEL
Date: 20220121

ACTIVE INGREDIENTS: ALCOHOL 0.7 mL/1 mL
INACTIVE INGREDIENTS: CARBOMER HOMOPOLYMER, UNSPECIFIED TYPE; GLYCERIN; PROPYLENE GLYCOL; .ALPHA.-TOCOPHEROL ACETATE; TROLAMINE; WATER

Hand Sanitizer

Active ingredient

Ethyl Alcohol 70% v/v

Purpose

Antiseptic

Use

For hand washing to decrease bacteria ont he skin.

Warnings

Flammable. Keep away from fire or flame.

For External Use Only

When using this product

avoid contact with eyes. If contact occurs rinse eyes thoroughly with water.

Stop use and ask a doctor

if skin irritation or rash develops and continues for more than 72 hours.

Keep out of reach of children.

If swallowed get medical help or contact your Poison Control right away.

Directions

- Place a palmful (5 grams) of product in one hand.
- Spread on both hands and rub into skin until dry (approximately 1 to 2 minutes).

Other information

- Do not store above 105°F,
- May discolor some fabrics.
- Harmful to wood finishes and plastics.

Inactive ingredients

Carbomer, Fragrance, Glycerin, Propylene Glycol, Tocopheryl Acetate, Triethanolamine, Water